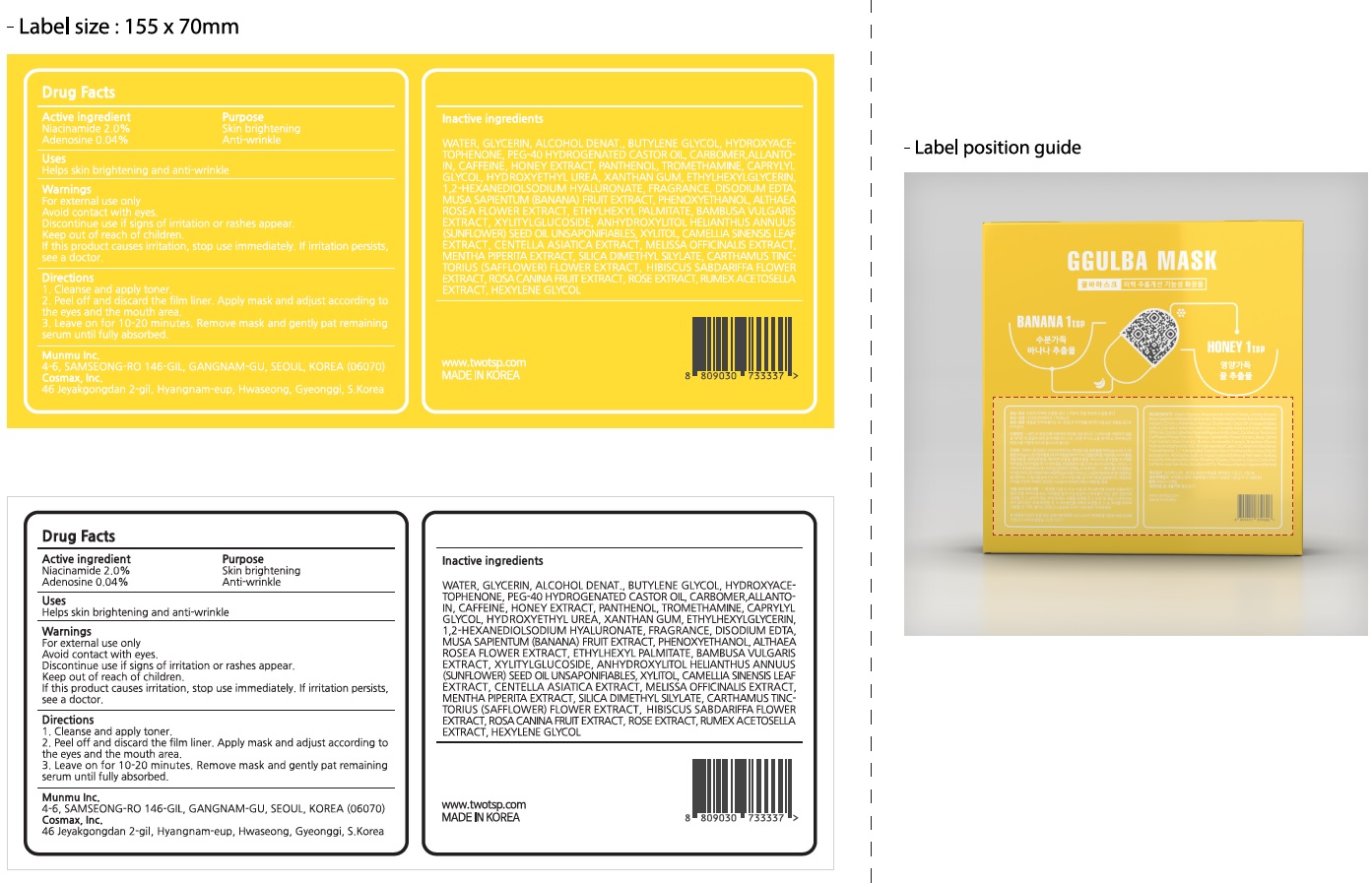 DRUG LABEL: GGULBA MASK
NDC: 72340-020 | Form: PATCH
Manufacturer: MUNMU INC
Category: otc | Type: HUMAN OTC DRUG LABEL
Date: 20210528

ACTIVE INGREDIENTS: Niacinamide 0.70 g/35 mL; Adenosine 0.01 g/35 mL
INACTIVE INGREDIENTS: WATER; GLYCERIN

ACTIVE INGREDIENTS

Niacinamide 2.0%, Adenosine 0.04%

INACTIVE INGREDIENTS

WATER, GLYCERIN, ALCOHOL DENAT., BUTYLENE GLYCOL, HYDROXYACETOPHENONE, PEG-40 HYDROGENATED CASTOR OIL, CARBOMER, ALLANTOIN, CAFFEINE, HONEY EXTRACT, PANTHENOL, TROMETHAMINE, CAPRYLYL GLYCOL, HYDROXYETHYL UREA, XANTHAN GUM, ETHYLHEXYLGLYCERIN, 1,2-HEXANEDIOL, SODIUM HYALURONATE, FRAGRANCE, DISODIUM EDTA, MUSA SAPIENTUM (BANANA) FRUIT EXTRACT, PHENOXYETHANOL, ALTHAEA ROSEA FLOWER EXTRACT, ETHYLHEXYL PALMITATE, BAMBUSA VULGARIS EXTRACT, XYLITYLGLUCOSIDE, ANHYDROXYLITOL HELIANTHUS ANNUUS (SUNFLOWER) SEED OIL UNSAPONIFIABLES, XYLITOL, CAMELLIA SINENSIS LEAF EXTRACT, CENTELLA ASIATICA EXTRACT, MELISSA OFFICINALIS EXTRACT, MENTHA PIPERITA EXTRACT, SILICA DIMETHYL SILYLATE, CARTHAMUS TINCTORIUS (SAFFLOWER) FLOWER EXTRACT, HIBISCUS SABDARIFFA FLOWER EXTRACT, ROSA CANINA FRUIT EXTRACT, ROSE EXTRACT, RUMEX ACETOSELLA EXTRACT, HEXYLENE GLYCOL

PURPOSE

Skin brightening, Anti-wrinkle

WARNINGS

For external use only
Avoid contact with eyes.
Discontinue use if signs of irritation or rashes appear.
Keep out of reach of children.
If this product causes irritation, stop use immediately. If irritation persists, see a doctor.

KEEP OUT OF REACH OF CHILDREN

Uses

■ Helps skin brightening and anti-wrinkle.

Directions

1. Cleanse and apply toner.
2. Peel off and discard the film liner. Apply mask and adjust according to the eyes and the mouth area.
3. Leave on for 10-20 minutes. Remove mask and gently pat remaining serum until fully absorbed.